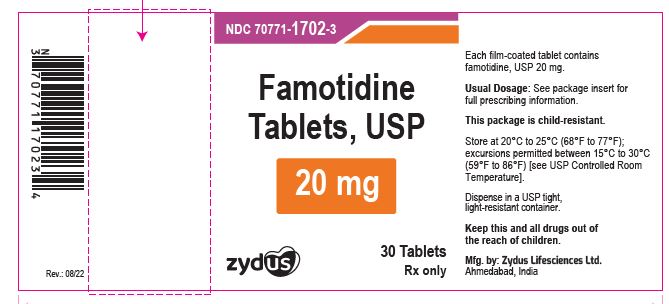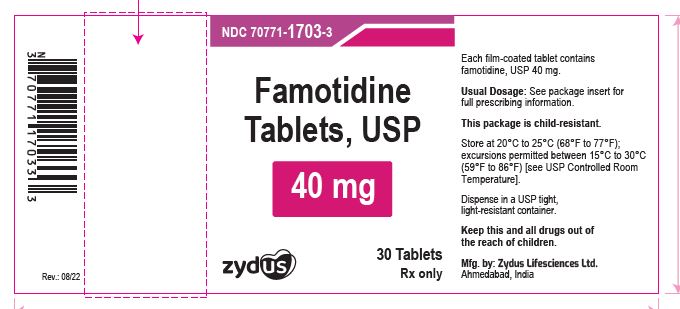 DRUG LABEL: Famotidine
NDC: 70771-1702 | Form: TABLET, FILM COATED
Manufacturer: Zydus Lifesciences Limited
Category: prescription | Type: HUMAN PRESCRIPTION DRUG LABEL
Date: 20241130

ACTIVE INGREDIENTS: FAMOTIDINE 20 mg/1 1
INACTIVE INGREDIENTS: HYPROMELLOSE 2910 (5 MPA.S); HYPROMELLOSE 2910 (6 MPA.S); MAGNESIUM STEARATE; MICROCRYSTALLINE CELLULOSE 101; MICROCRYSTALLINE CELLULOSE 102; POLYETHYLENE GLYCOL 8000; SILICON DIOXIDE; SODIUM STARCH GLYCOLATE TYPE A; STARCH, CORN; TALC; TITANIUM DIOXIDE

Famotidine Tablets, USP

PACKAGE LABEL.PRINCIPAL DISPLAY PANEL

NDC 70771-1702-3

Famotidine Tablets USP, 20 mg

30 Tablets

Rx only

NDC 70771-1703-3

Famotidine Tablets USP, 40 mg

30 Tablets

Rx only